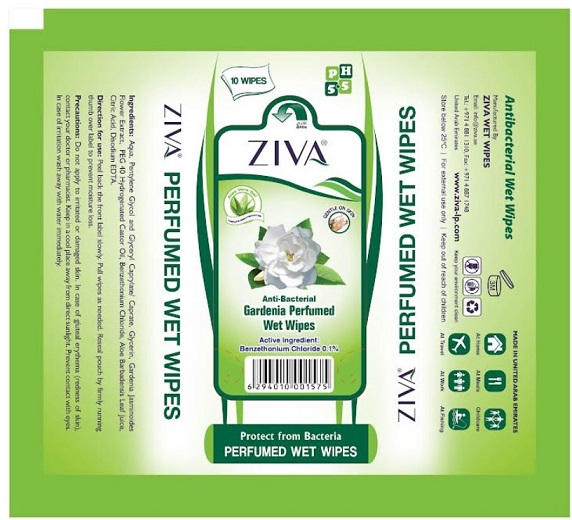 DRUG LABEL: ZIVA PERFUMED WIPES GARDENIA
NDC: 81450-007 | Form: CLOTH
Manufacturer: Ziva Wetwipes FZCo
Category: otc | Type: HUMAN OTC DRUG LABEL
Date: 20231005

ACTIVE INGREDIENTS: BENZETHONIUM CHLORIDE 0.1 g/100 mL
INACTIVE INGREDIENTS: CITRIC ACID MONOHYDRATE; WATER; ALOE VERA LEAF; GARDENIA JASMINOIDES FLOWER; HYDROGENATED CASTOR OIL; GLYCERYL CAPRYLATE/CAPRATE; PENTYLENE GLYCOL; GLYCERIN; EDETATE DISODIUM

Drug Facts

Active Ingredient:

Benzethonium Chloride 0.1%

Direction for use

Peel back the front label slowly. Pull wipes as needed. Reseal pouch by firmly running thumb over label to prevent moisture loss.

Precautions:

For external use only. Do not apply to irritated or damaged skin. In case of gluteal erythema (redness of skin), contact your doctor or pharmacist. Keep in a cool place away from direct sunlight. Prevent contact with eyes. In case of irritation wash away with water immediately.

Other information

Store below 25°C

Ingredients:

Aqua, Pentylene Glycol and Glyceryl Caprylate / Caprate, Perfume, PEG 40 Hydrogenated Castor Oil, Benzethonium Chloride, Aloe Barbadensis Leaf Juice, Citric Acid, Disodium EDTA.